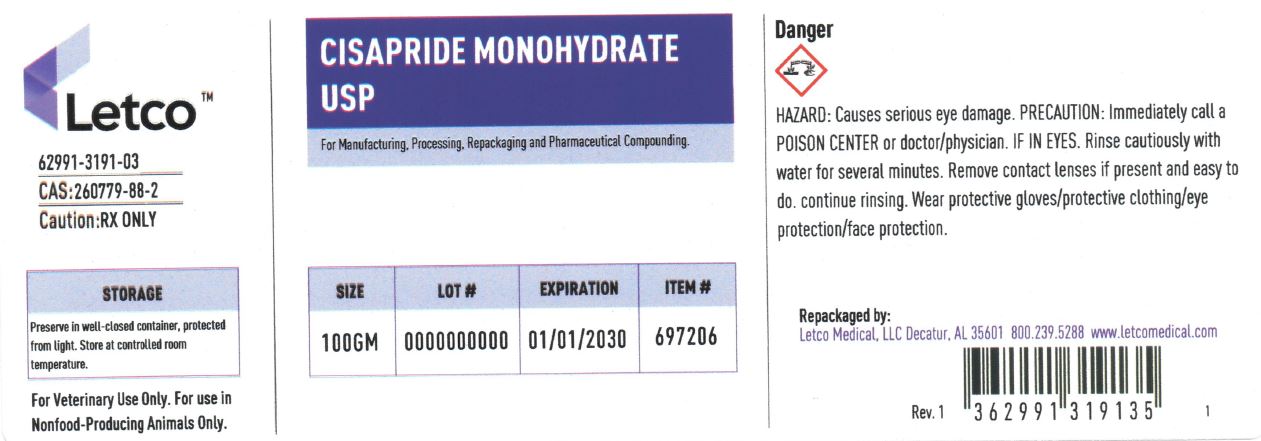 DRUG LABEL: CISAPRIDE MONOHYDRATE
NDC: 62991-3191 | Form: POWDER
Manufacturer: LETCO MEDICAL, LLC
Category: other | Type: BULK INGREDIENT - ANIMAL DRUG
Date: 20240718

ACTIVE INGREDIENTS: CISAPRIDE MONOHYDRATE 1 g/1 g

CISAPRIDE MONOHYDRATE USP

PACKAGE LABEL

Cisapride Monohydrate USP 100gm